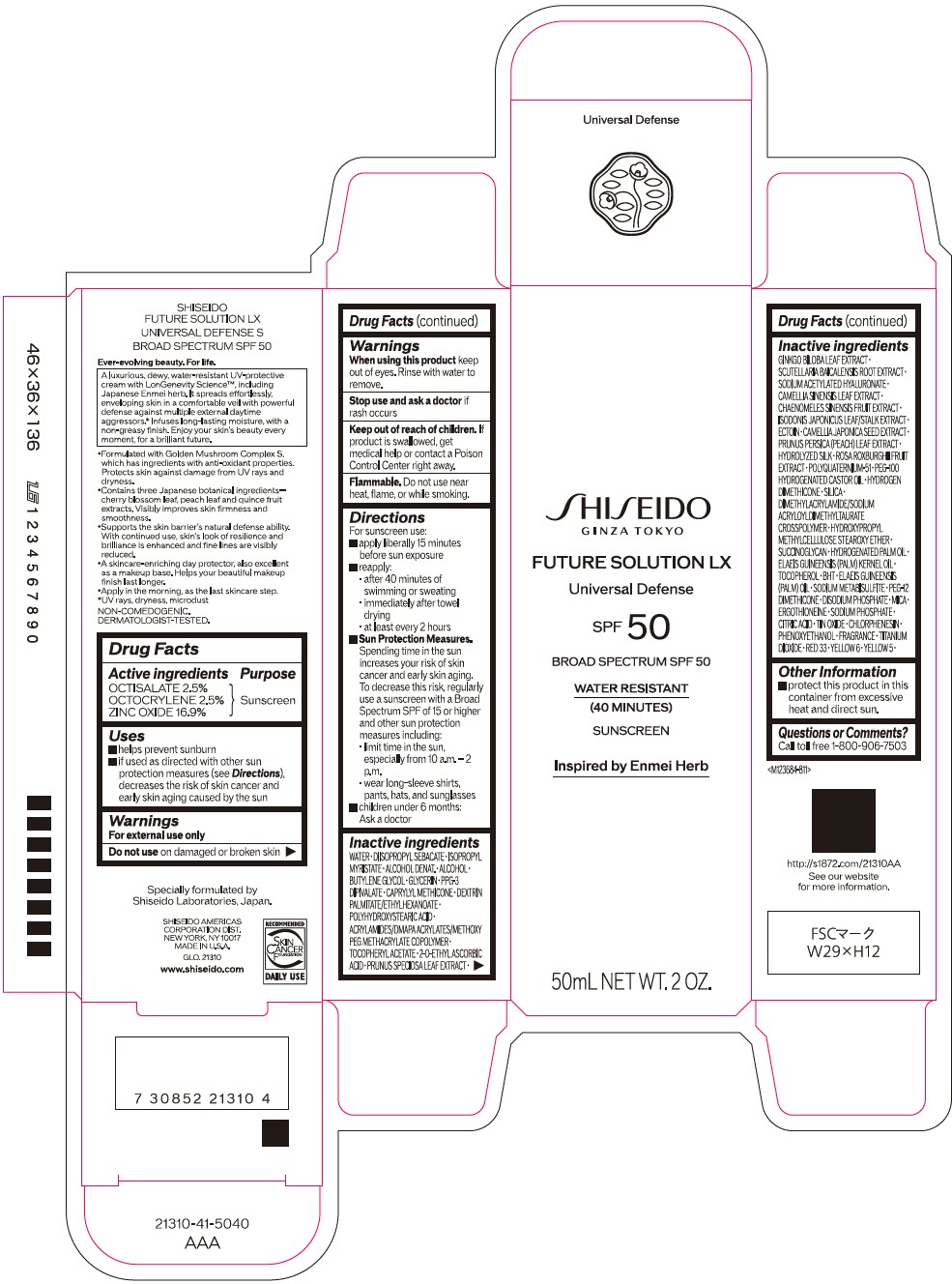 DRUG LABEL: SHISEIDO FUTURE LX UNIVERSAL DEFENSE S
NDC: 58411-902 | Form: CREAM
Manufacturer: SHISEIDO AMERICAS CORPORATION
Category: otc | Type: HUMAN OTC DRUG LABEL
Date: 20260128

ACTIVE INGREDIENTS: OCTISALATE 1.44 g/50 mL; OCTOCRYLENE 1.44 g/50 mL; ZINC OXIDE 9.7 g/50 mL
INACTIVE INGREDIENTS: WATER; DIISOPROPYL SEBACATE; ISOPROPYL MYRISTATE; ALCOHOL; BUTYLENE GLYCOL; GLYCERIN; CAPRYLYL TRISILOXANE; POLYHYDROXYSTEARIC ACID (2300 MW); .ALPHA.-TOCOPHEROL ACETATE, DL-; 2-O-ETHYL ASCORBIC ACID; PRUNUS SPECIOSA LEAF; GINKGO; SCUTELLARIA BAICALENSIS ROOT; SODIUM ACETYLATED HYALURONATE; GREEN TEA LEAF; CHAENOMELES SINENSIS FRUIT; CAMELLIA JAPONICA SEED OIL; PRUNUS PERSICA LEAF; ROSA ROXBURGHII FRUIT; POLYQUATERNIUM-51 (2-METHACRYLOYLOXYETHYL PHOSPHORYLCHOLINE/N-BUTYL METHACRYLATE; 3:7); HYDROGEN DIMETHICONE (13 CST); SILICON DIOXIDE; HYDROGENATED PALM OIL; PALM KERNEL OIL; .ALPHA.-TOCOPHEROL; BUTYLATED HYDROXYTOLUENE; PALM OIL; SODIUM METABISULFITE; PEG-12 DIMETHICONE (300 CST); SODIUM PHOSPHATE, DIBASIC, ANHYDROUS; MICA; ERGOTHIONEINE; SODIUM PHOSPHATE; CITRIC ACID ACETATE; STANNIC OXIDE; CHLORPHENESIN; PHENOXYETHANOL; TITANIUM DIOXIDE; D&C RED NO. 33; FD&C YELLOW NO. 5; FD&C YELLOW NO. 6

SHISEIDO FUTURE LX UNIVERSAL DEFENSE S

Drug Facts

ACTIVE INGREDIENT

Active ingredients | Purpose
OCTISALATE 2.5% | Sunscreen
OCTOCRYLENE 2.5% | Sunscreen
ZINC OXIDE 16.9% | Sunscreen

Uses

- helps prevent sunburn
- if used as directed with other sun protection measures (see Directions), decreases the risk of skin cancer and early skin aging caused by the sun

Warnings

For external use only

Do not useon damaged or broken skin

WHEN USING

When using this productkeep out of eyes. Rinse with water to remove.

Stop use and ask a doctorif rash occurs.

Keep out of reach of children.If product is swallowed, get medical help or contact a Poison Control Center right away.

Directions

For sunscreen use:

- apply liberally 15 minutes before sun exposure
- use a water resistant sunscreen if swimming or sweating
- reapply at least every 2 hours
- Sun Protection Measures. Spending time in the sun increases your risk of skin cancer and early skin aging. To decrease this risk, regularly use a sunscreen with a Broad Spectrum SPF of 15 or higher and other sun protection measures including:
  - limit time in the sun, especially from 10 a.m. – 2 p.m.
  - wear long-sleeve shirts, pants, hats, and sunglasses
- children under 6 months: Ask a doctor

Inactive Ingredients

WATER･DIISOPROPYL SEBACATE･ISOPROPYL MYRISTATE･ALCOHOL DENAT.･ALCOHOL･BUTYLENE GLYCOL･GLYCERIN･PPG-3 DIPIVALATE･CAPRYLYL METHICONE･DEXTRIN PALMITATE/ETHYLHEXANOATE･POLYHYDROXYSTEARIC ACID･ACRYLAMIDES/DMAPA ACRYLATES/METHOXY PEG METHACRYLATE COPOLYMER･TOCOPHERYL ACETATE･2-O-ETHYL ASCORBIC ACID･PRUNUS SPECIOSA LEAF EXTRACT･GINKGO BILOBA LEAF EXTRACT･SCUTELLARIA BAICALENSIS ROOT EXTRACT･SODIUM ACETYLATED HYALURONATE･CAMELLIA SINENSIS LEAF EXTRACT･CHAENOMELES SINENSIS FRUIT EXTRACT･ISODONIS JAPONICUS LEAF/STALK EXTRACT･ECTOIN･CAMELLIA JAPONICA SEED EXTRACT･PRUNUS PERSICA (PEACH) LEAF EXTRACT･HYDROLYZED SILK･ROSA ROXBURGHII FRUIT EXTRACT･POLYQUATERNIUM-51･PEG-100 HYDROGENATED CASTOR OIL･HYDROGEN DIMETHICONE･SILICA･DIMETHYLACRYLAMIDE/SODIUM ACRYLOYLDIMETHYLTAURATE CROSSPOLYMER･HYDROXYPROPYL METHYLCELLULOSE STEAROXY ETHER･SUCCINOGLYCAN･HYDROGENATED PALM OIL･ELAEIS GUINEENSIS (PALM) KERNEL OIL･TOCOPHEROL･BHT･ELAEIS GUINEENSIS (PALM) OIL･SODIUM METABISULFITE･PEG-12 DIMETHICONE･DISODIUM PHOSPHATE･MICA･ERGOTHIONEINE･SODIUM PHOSPHATE･CITRIC ACID･TIN OXIDE･CHLORPHENESIN･PHENOXYETHANOL･FRAGRANCE･TITANIUM DIOXIDE･RED 33･YELLOW 6･YELLOW 5･

Other information

- protect this product in this container from excessive heat and direct sun.

Questions or comments?

Call toll free 1-800-906-7503

PRINCIPAL DISPLAY PANEL - 50 mL Tube Carton

SHISEIDO
GINZA TOKYO

FUTURE SOLUTION LX

Universal Defense

SPF 50

BROAD SPECTRUM SPF 50

WATER RESISTANT
(40 MINUTES)

SUNSCREEN

Inspired by Enmei Herb

50mL NET WT. 2 OZ.